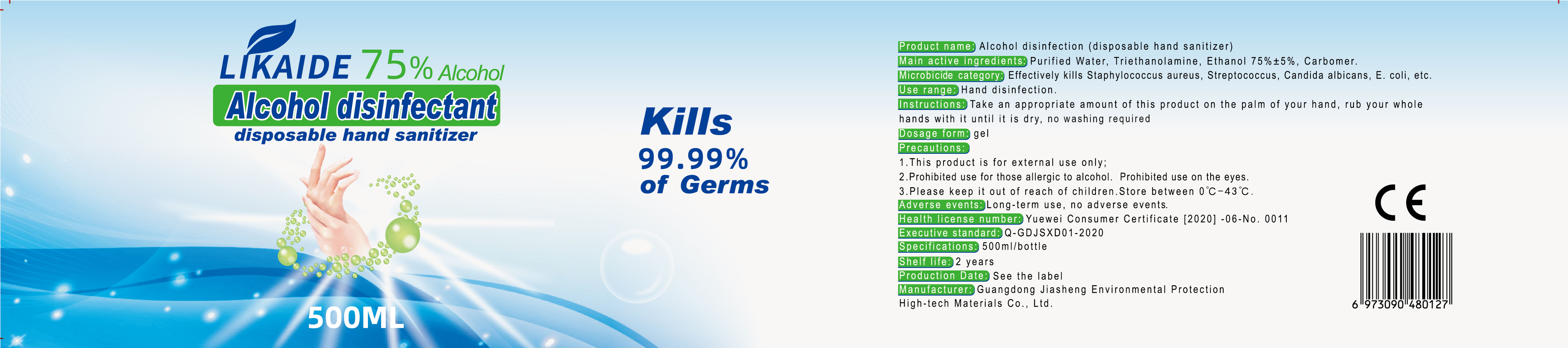 DRUG LABEL: Alcohol disinfectant(disposable hand sanitizer)
NDC: 54644-002 | Form: GEL
Manufacturer: Guangdong Jiasheng Environmental Protection High-Tech Material Co.,Ltd.
Category: otc | Type: HUMAN OTC DRUG LABEL
Date: 20200415

ACTIVE INGREDIENTS: ALCOHOL 375 mL/500 mL
INACTIVE INGREDIENTS: TROLAMINE; CARBOMER HOMOPOLYMER, UNSPECIFIED TYPE; WATER

DOSAGE AND ADMINISTRATION

keep it out of reach of children. Store between 0°C-43 C .

INACTIVE INGREDIENT

Purified Water

Triethanolamine

Carbomer.

INDICATIONS AND USAGE

Take an appropriate amount of this product on the palm of your hand, rub your whole hands with it until it is dry, no washing required

ACTIVE INGREDIENT

Ethanol

keep out of children

PURPOSE

Disinfection
Sterilization

WARNINGS

1.This product is for external use only.
2. Prohibited use for those allergic to alcohol. Prohibited use on the eyes.
3.Please keep it out of reach of children.Store between 0°C-43 C.